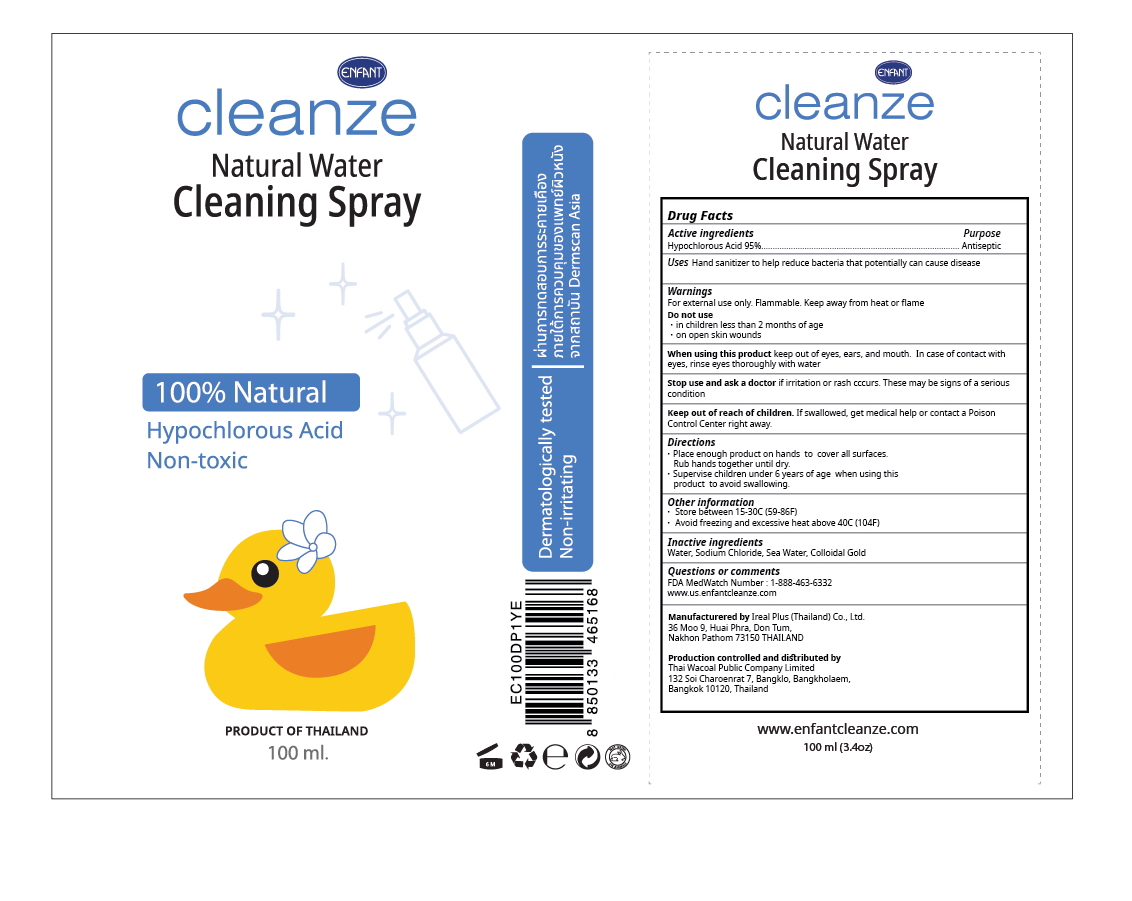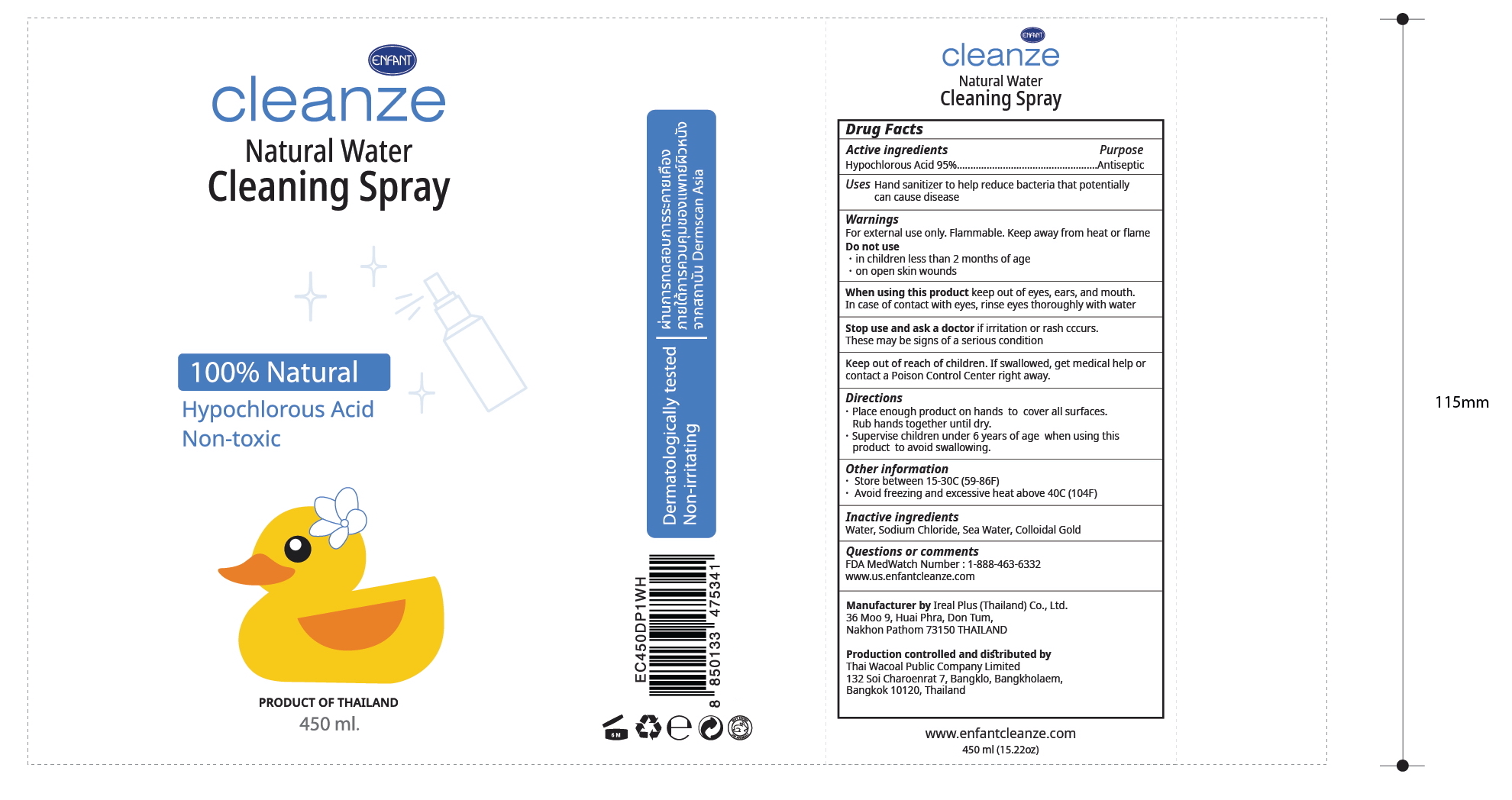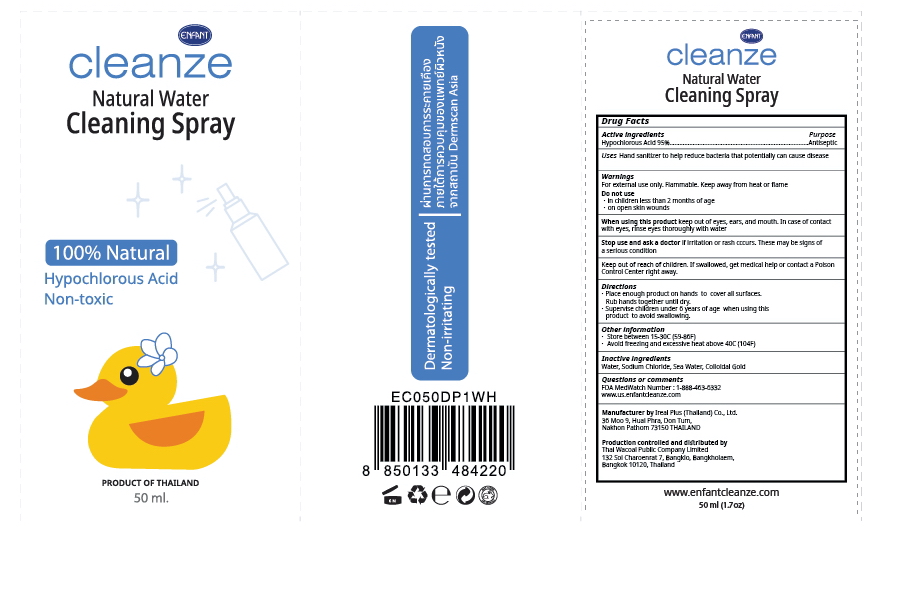 DRUG LABEL: Hand sanitizer
NDC: 79841-001 | Form: SOLUTION
Manufacturer: THAI WACOAL PUBLIC COMPANY LIMITED
Category: otc | Type: HUMAN OTC DRUG LABEL
Date: 20200731

ACTIVE INGREDIENTS: HYPOCHLOROUS ACID 95 mg/100 mL
INACTIVE INGREDIENTS: GOLD; SODIUM CHLORIDE; MERCURY; WATER

Active Ingredient(s)

Hypochlorous Acid 95% v/v.

Purpose

Purpose: Antiseptic

Use

Hand Sanitizer to help reduce bacteria that potentially can cause disease.

Warnings

For external use only. Flammable. Keep away from heat or flame

Do not use

- in children less than 2 months of age
- on open skin wounds

When using this product keep out of eyes, ears, and mouth. In case of contact with eyes, rinse eyes thoroughly with water.

Stop use and ask a doctor if irritation or rash occurs. These may be signs of a serious condition.

Keep out of reach of children. If swallowed, get medical help or contact a Poison Control Center right away.

Directions

- Place enough product on hands to cover all surfaces. Rub hands together until dry.
- Supervise children under 6 years of age when using this product to avoid swallowing.

Other information

- Store between 15-30C (59-86F)
- Avoid freezing and excessive heat above 40C (104F)

Inactive ingredients

Water, Sodium Chloride, Seawater, Collodial Gold

Package Label - Principal Display Panel

50mL NDC:79841 -001-05

100 mL NDC:79841 -001-10

450 mL NDC:79841 -001-45